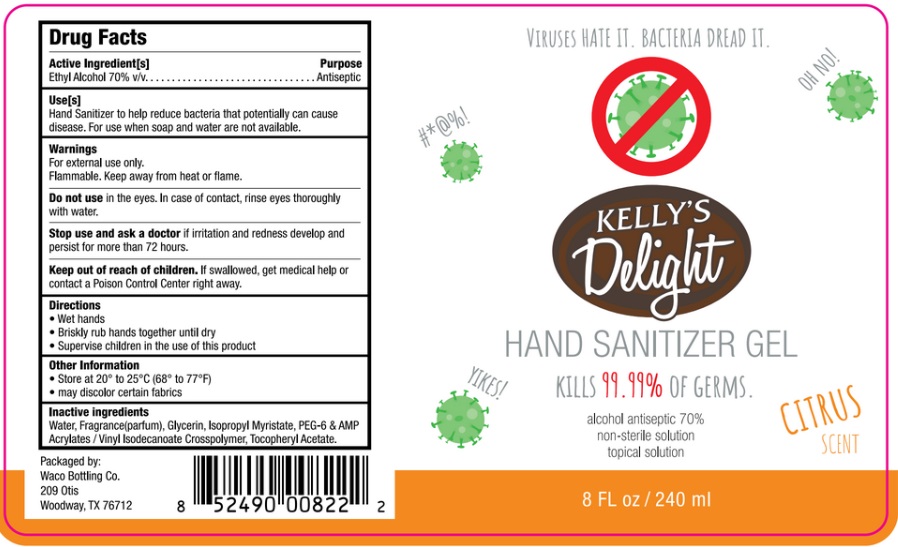 DRUG LABEL: Kellys Delight Hand Sanitizer
NDC: 79175-002 | Form: GEL
Manufacturer: WACO BOTTLING LLC
Category: otc | Type: HUMAN OTC DRUG LABEL
Date: 20221114

ACTIVE INGREDIENTS: ALCOHOL 70 mL/100 mL
INACTIVE INGREDIENTS: GLYCERIN; ISOPROPYL MYRISTATE; POLYETHYLENE GLYCOL 300; ADENOSINE PHOSPHATE; ACRYLATES/VINYL ISODECANOATE CROSSPOLYMER (10000 MPA.S NEUTRALIZED AT 0.5%); ALPHA-TOCOPHEROL ACETATE; DIPROPYLENE GLYCOL; LEMON OIL; LINALYL ACETATE; LINALOOL, (+/-)-; GERANIOL; TERPINEOL; CITRAL; 4-TERT-BUTYLCYCLOHEXYL ACETATE; .BETA.-CITRONELLOL, (+/-)-

Active Ingredient

Ethyl Alcohol 70% v/v.

Purpose

Antiseptic

Use

Hand Sanitizer to help reduce bacteria that potentially can cause disease.

For use when soap and water are not available.

Warnings

For external use only.

Flammable. Keep away from heat or flame

Do not use in the eyes. In case of contact, rinse eyes thoroughly with water.

Stop use and ask a doctor if irritation and redness develop and persist for more than 72 hours.

Keep out of reach of children. If swallowed, get medical help or contact a Poison Control Center right away.

Directions

- Wet hands.
- Briskly rub hands together until dry.
- Supervise children in the use of this product.

Other information

- Store at 20-25^0C(68-77^0F)
- Avoid freezing and excessive heat above 40C (104F)

Inactive ingredients

Water, Fragrance (Parfum), Glycerin, lsopropyl Myristate, PEG-6 & AMP Acrylates I Vinyl lsodecanoate Crosspolymer, Tocopheryl Acetate.